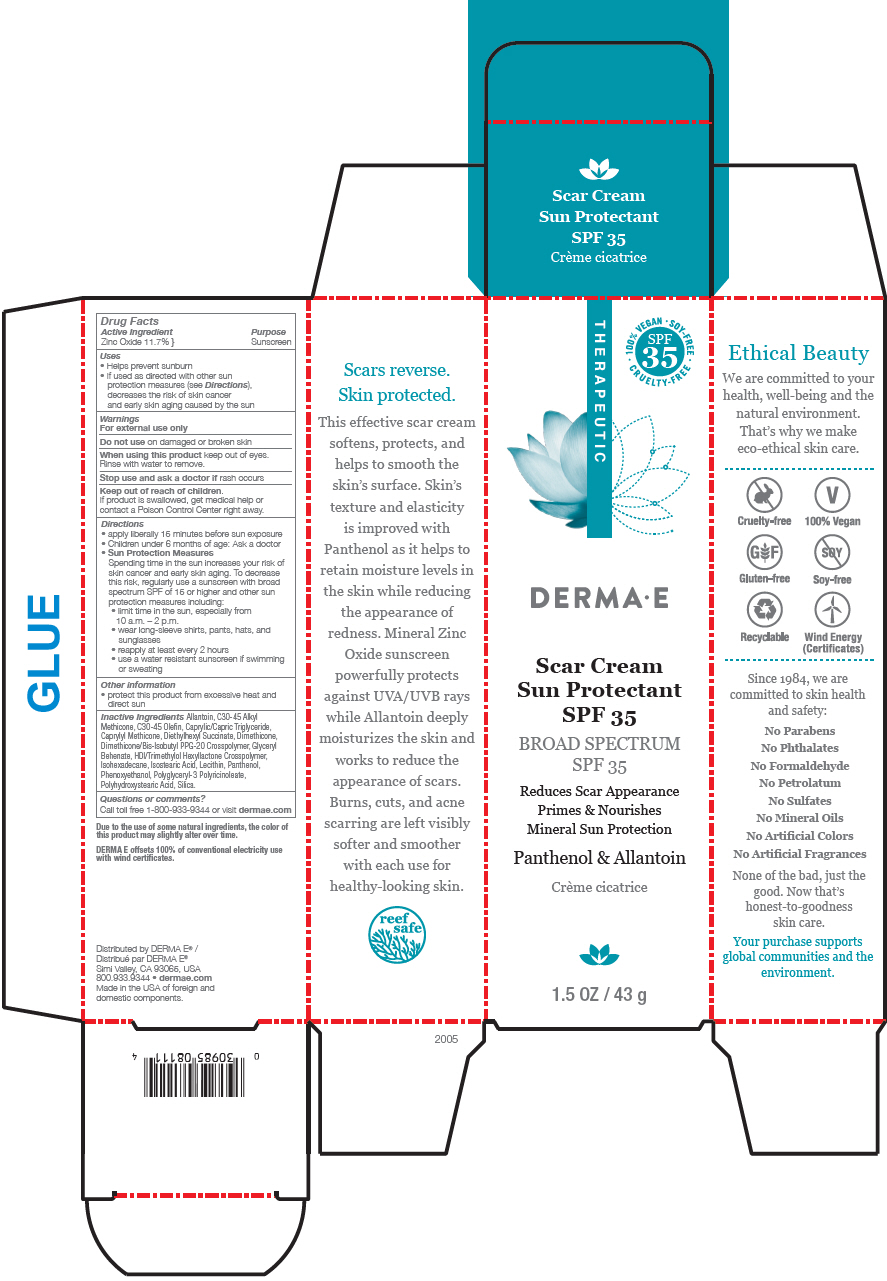 DRUG LABEL: Scar Gel
NDC: 54108-8111 | Form: CREAM
Manufacturer: derma e
Category: otc | Type: HUMAN OTC DRUG LABEL
Date: 20240717

ACTIVE INGREDIENTS: ZINC OXIDE 117 mg/1 g
INACTIVE INGREDIENTS: ALLANTOIN; C30-45 ALKYL METHICONE; C30-45 OLEFIN; MEDIUM-CHAIN TRIGLYCERIDES; CAPRYLYL TRISILOXANE; DIETHYLHEXYL SUCCINATE; DIMETHICONE; DIMETHICONE/BIS-ISOBUTYL PPG-20 CROSSPOLYMER; GLYCERYL DIBEHENATE; HEXAMETHYLENE DIISOCYANATE/TRIMETHYLOL HEXYLLACTONE CROSSPOLYMER; ISOHEXADECANE; ISOSTEARIC ACID; LECITHIN, SUNFLOWER; PANTHENOL; PHENOXYETHANOL; POLYGLYCERYL-3 PENTARICINOLEATE; POLYHYDROXYSTEARIC ACID STEARATE; SILICON DIOXIDE

Scar Gel
SPF 35

Drug Facts

Active Ingredient

Zinc Oxide 11.7% }

Purpose

Sunscreen

Uses

- Helps prevent sunburn
- If used as directed with other sun protection measures (see Directions), decreases the risk of skin cancer and early skin aging caused by the sun

Warnings

For external use only

Do not use on damaged or broken skin

When using this product keep out of eyes. Rinse with water to remove.

Stop use and ask a doctor if rash occurs

Keep out of reach of children.

If product is swallowed, get medical help or contact a Poison Control Center right away.

Directions

- apply liberally 15 minutes before sun exposure
- Children under 6 months of age: Ask a doctor
- Sun Protection Measures
  Spending time in the sun increases your risk of skin cancer and early skin aging. To decrease this risk, regularly use a sunscreen with broad spectrum SPF of 15 or higher and other sun protection measures including:
  - limit time in the sun, especially from 10 a.m. – 2 p.m.
  - wear long-sleeve shirts, pants, hats, and sunglasses
  - reapply at least every 2 hours
  - use a water resistant sunscreen if swimming or sweating

Other information

- protect this product from excessive heat and direct sun

Inactive Ingredients

Allantoin, C30-45 Alkyl Methicone, C30-45 Olefin, Caprylic/Capric Triglyceride, Caprylyl Methicone, Diethylhexyl Succinate, Dimethicone, Dimethicone/Bis-Isobutyl PPG-20 Crosspolymer, Glyceryl Behenate, HDI/Trimethylol Hexyllactone Crosspolymer, Isohexadecane, Isostearic Acid, Lecithin, Panthenol, Phenoxyethanol, Polyglyceryl-3 Polyricinoleate, Polyhydroxystearic Acid, Silica.

Questions or comments?

Call toll free 1-800-933-9344 or visit dermae.com

Distributed by DERMA E®
Simi Valley, CA 93065, USA

PRINCIPAL DISPLAY PANEL - 43 g Tube Box

THERAPEUTIC

• 100% VEGAN • SOY-FREE •
SPF
35
CRUELTY-FREE

DERMA•E

Scar Cream
Sun Protectant
SPF 35

BROAD SPECTRUM
SPF 35

Reduces Scar Appearance
Primes & Nourishes
Mineral Sun Protection

Panthenol & Allantoin

1.5 OZ / 43 g